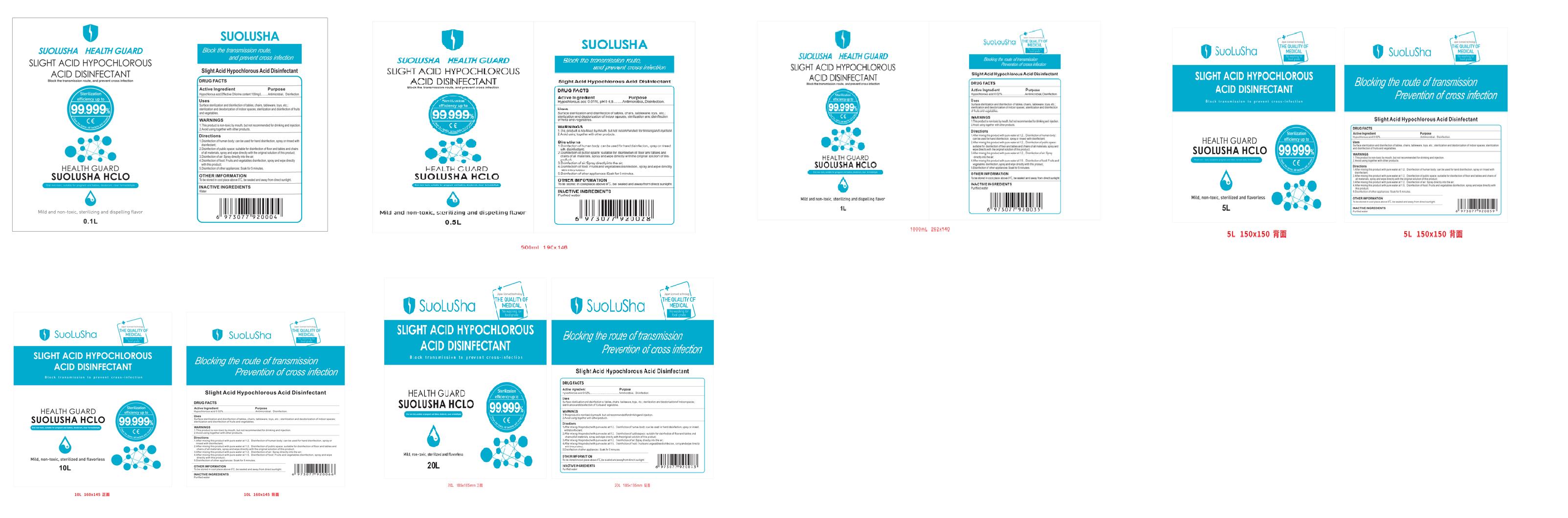 DRUG LABEL: Slight Acid Hypochlorous Acid Disinfectant
NDC: 75437-001 | Form: LIQUID
Manufacturer: Guangdong Huarui Technology Co., Ltd.
Category: otc | Type: HUMAN OTC DRUG LABEL
Date: 20200428

ACTIVE INGREDIENTS: HYPOCHLOROUS ACID 100 mg/100 L
INACTIVE INGREDIENTS: WATER

Active Ingredient(s)

Hypochlorous acid 100mg/L

Purpose

Antimicrobial disnfection

Use

Surface sterilization and disinfection of tables, chairs, tableware, toys, etcsteilization and dodo zaon of indoor spaces tilization and disinfection of fruitsand vegetables

Warnings

This product is non-toxic by mouth, but not recommended for drinking and injectio2. Avoid using together with other products

Do not use

、

When using this product keep out of eyes, ears, and mouth. In case of contact with eyes, rinse eyes thoroughly with water.
Stop use and ask a doctor if irritation or rash occurs. These may be signs of a serious condition.
Keep out of reach of children. If swallowed, get medical help or contact a Poison Control Center right away.

Stop use and ask a doctor if irritation or rash occurs.

Keep out of reach of children

Directions

1. Disinfection of human body. can be used for hand disinfection, spray or rinsed withdisinfectant:2. Disinfection of public space suitable for disinfection of floor and tables and chairsof all materials, spray and wipe directly with the orginal solution of this product.3. Disinfection of air: Spray directly into the air.4. Disinfection of food: Fruits and vegetables disinfection, spray and wipe directlywith this product:5. Disinfection of other appliances: Soak for 5 minutes

Other information

- OTHER IMFORMATIONTo be stored in cool place above 0 C, be sealed and away from direct sunlight

Inactive ingredients

Water